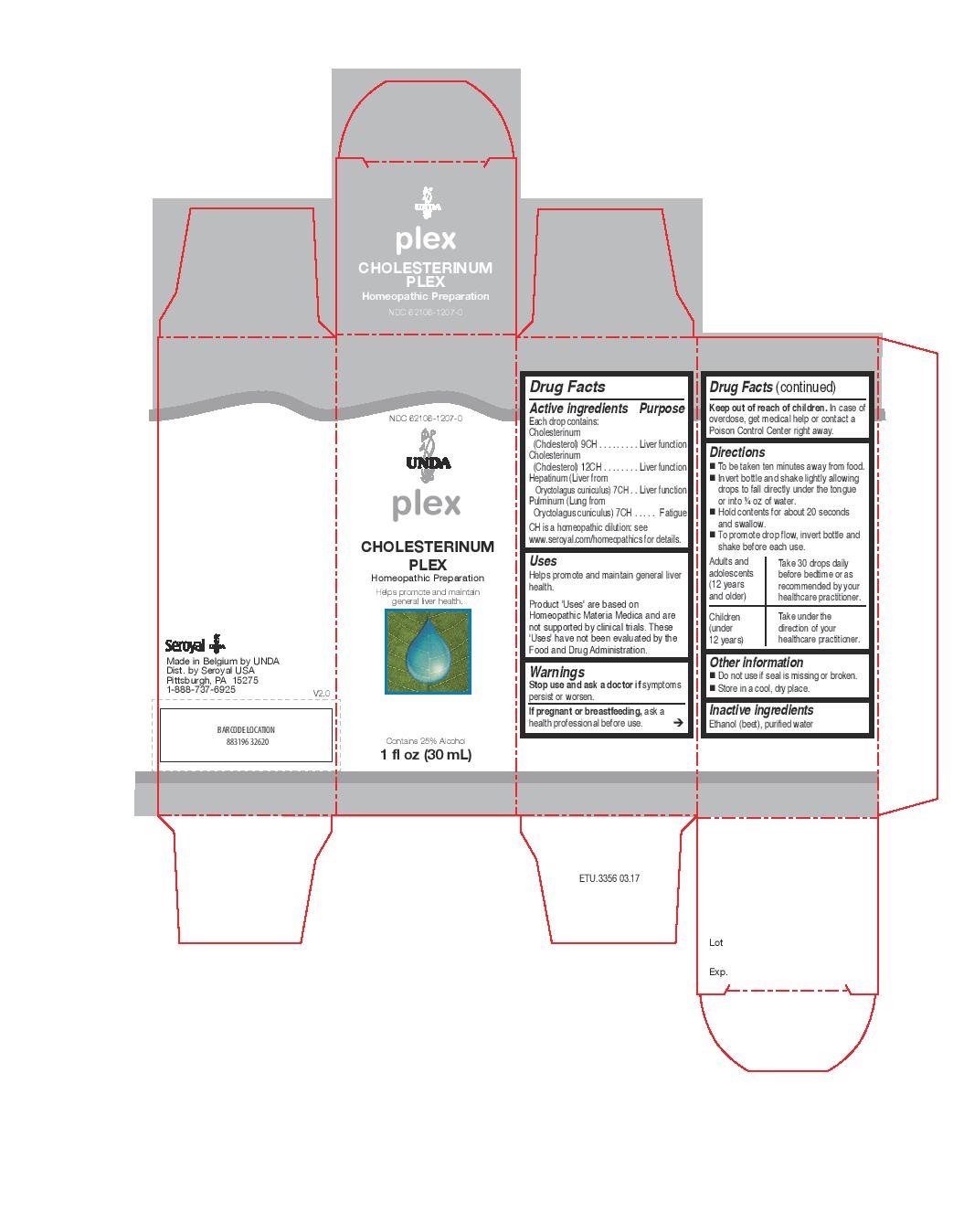 DRUG LABEL: CHOLESTERINUM PLEX
NDC: 62106-1207 | Form: LIQUID
Manufacturer: Seroyal USA
Category: homeopathic | Type: HUMAN OTC DRUG LABEL
Date: 20221109

ACTIVE INGREDIENTS: CHOLESTEROL 9 [hp_C]/30 mL; ORYCTOLAGUS CUNICULUS LIVER 7 [hp_C]/30 mL; ORYCTOLAGUS CUNICULUS LUNG 7 [hp_C]/30 mL
INACTIVE INGREDIENTS: ALCOHOL; WATER

CHOLESTERINUM PLEX

Active ingredients
Each drop contains:
Cholesterinum (Cholesterol) 9CH
Cholesterinum (Cholesterol) 12CH
Hepatinum (Liver from Oryctolagus cuniculus) 7CH
Pulminum (Lung from Oryctolagus cuniculus) 7CH

Uses
Helps promote and maintain general liver health.

Warnings
Stop use and ask a doctor if symptoms persist or worsen.
If pregnant or breastfeeding, ask ahealth professional before use.

Keep out of reach of children. In case ofoverdose, get medical help or contact a
Poison Control Center right away.

Keep out of reach of children. In case of overdose, get medical help or contact a Poison Control Center right away.

PREGNANCY OR BREAST FEEDING

If pregnant or breastfeeding, ask a health professional before use.

Other information
Do not use if seal is missing or broken.
Store in a cool, dry place.

Inactive ingredients
Ethanol (beet), purified water

Directions
To be taken ten minutes away from food.
Invert bottle and shake lightly allowing drops to fall directly under the tongue or into ¼ oz of water.
Hold contents for about 20 seconds and swallow.
To promote drop flow, invert bottle and shake before each use.

Adults and adolescents (12 years and older)

Take 30 drops daily before bedtime or as recommended by your healthcare practitioner.

Children (under 12 years)

Take under the direction of your healthcare practitioner.

Uses
Helps promote and maintain general liver health.

Directions
To be taken ten minutes away from food.
Invert bottle and shake lightly allowing drops to fall directly under the tongue or into ¼ oz of water.
Hold contents for about 20 seconds and swallow.
To promote drop flow, invert bottle and shake before each use.

Adults and adolescents (12 years and older)

Take 30 drops daily before bedtime or as recommended by your healthcare practitioner.

Children (under 12 years)

Take under the direction of your healthcare practitioner.

PACKAGE LABEL

NDC 62106-1207-0

UNDA

plex

CHOLESTERINUM PLEX

Homeopathic Preparation

Helps promote and maintain general liver health.

Contains 25% Alcohol

1 fl oz (30 mL)